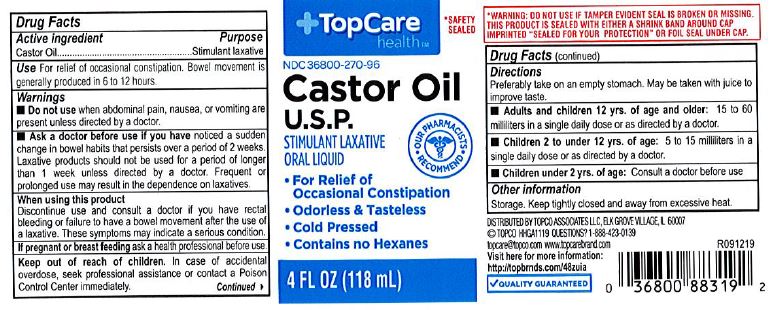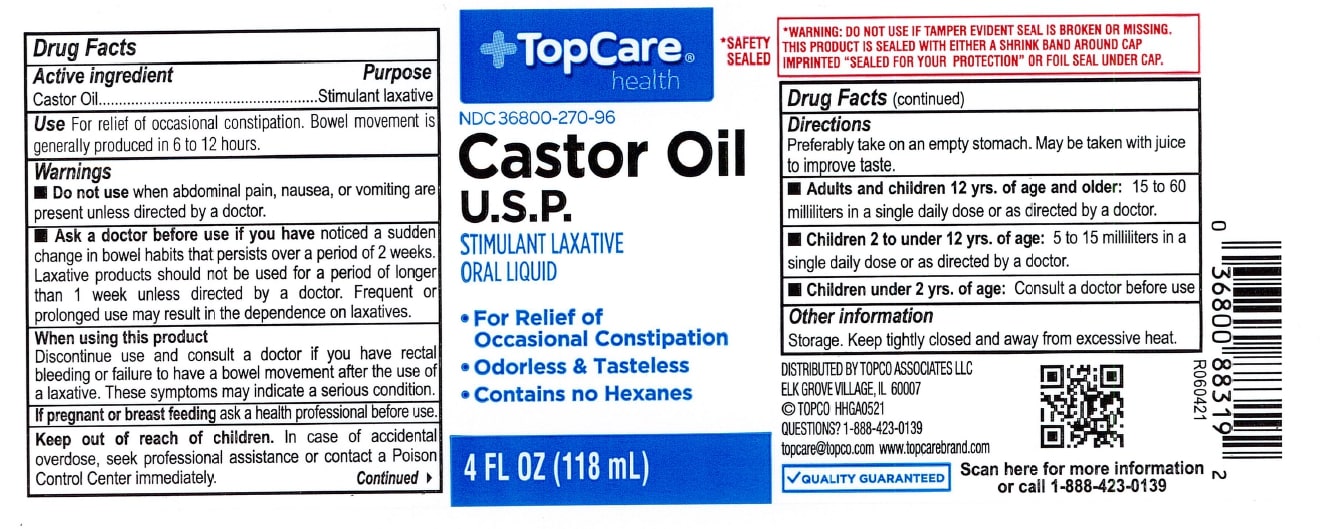 DRUG LABEL: Top Care Castor Oil
NDC: 36800-270 | Form: OIL
Manufacturer: TOPCO ASSOCIATES LLC
Category: otc | Type: HUMAN OTC DRUG LABEL
Date: 20231218

ACTIVE INGREDIENTS: CASTOR OIL 1 mg/1 mL
INACTIVE INGREDIENTS: WATER

Top Care Castor Oil, USP

ACTIVE INGREDIENT

Castor Oil

PURPOSE

Stimulant Laxative

INDICATIONS AND USAGE

For relief of occasional constipation. Bowel movement is generally produced in 6 to 12 hours.

Do not use when abdominal pain, nausea, or vomiting are present unless directed by a doctor.

KEEP OUT OF REACH OF CHILDREN

In case of accidental overdose, seek profssional assistance or contact a Poison Control Center immediately.

DOSAGE AND ADMINISTRATION

Preferably take on an empty stomach. May be taken with juice to improve taste.

Adults and children 12 yrs. of age and older: 15 to 60 milliliters in a single daily dose or as directed by a doctor.

Children 2 to under 12 yrs. of age: 5 to 15 milliliters in a single dose or as directed by a doctor.

Children under 2 yrs. of age: Consult a doctor before use.

RECENT MAJOR CHANGES

Changed 1 to 4 tablesponfuls to 15 to 60 milliliters, changed 1 to 3 teaspoonfuls to 5 to 15 milliliters. (6/2021)

INACTIVE INGREDIENT

None